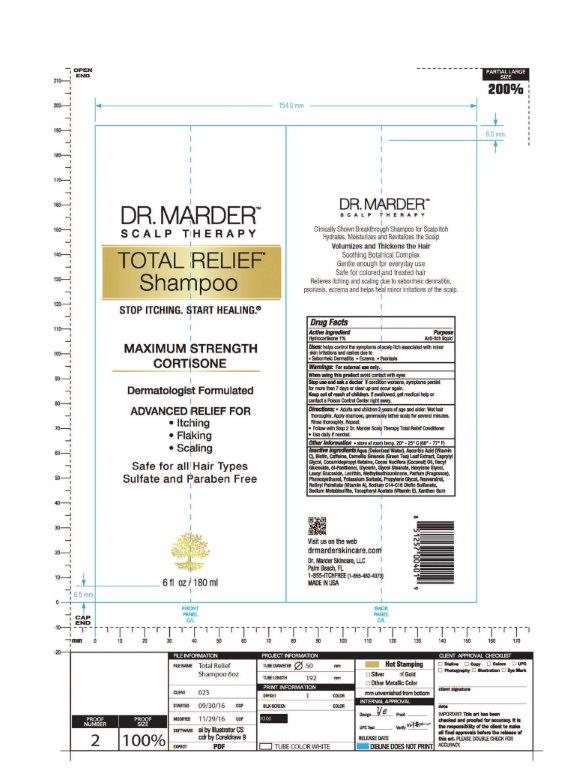 DRUG LABEL: Hydrocortisone
NDC: 71516-001 | Form: SHAMPOO
Manufacturer: Dr Marder Skincare LLC
Category: otc | Type: HUMAN OTC DRUG LABEL
Date: 20191102

ACTIVE INGREDIENTS: HYDROCORTISONE 1 g/100 mL
INACTIVE INGREDIENTS: GLYCOL STEARATE; HEXYLENE GLYCOL; POTASSIUM SORBATE; SODIUM C14-16 OLEFIN SULFONATE; WATER; ASCORBIC ACID; BIOTIN; CAFFEINE; CAMELLIA SINENSIS SEED OIL; CAPRYLYL GLYCOL; COCAMIDOPROPYL BETAINE; COCONUT OIL; DECYL GLUCOSIDE; PANTHENOL; GLYCERIN; LAURYL GLUCOSIDE; LECITHIN, SOYBEAN; METHYLISOTHIAZOLINONE; PHENOXYETHANOL; PROPYLENE GLYCOL; RESVERATROL; VITAMIN A PALMITATE; SODIUM METABISULFITE; ALPHA-TOCOPHEROL ACETATE; XANTHAN GUM

Dr. Marder Scalp Therapy Total Relief Shampoo

DOSAGE AND ADMINISTRATION

Wet hair thoroughly. apply shampoo, generously lather scalp for several minutes. Rinse thoroughly. repeat.Follow with Step 2 Dr. Marder Scalp Therapy total Relief Conditioner. Use Daily if needed.

WARNINGS

For external use only.

When using this product avoid contact with eyes.

ACTIVE INGREDIENT

Hydrocortisone 1%

INACTIVE INGREDIENT

HEXYLENE GLYCOL

POTASSIUM SORBATE

SODIUM C14-16 OLEFIN SULFONATE

WATER

ASCORBIC ACID

BIOTIN

CAFFEINE

CAMELLIA SINENSIS SEED OIL

CAPRYLYL GLYCOL

COCAMIDOPROPYL BETAINE

XANTHAN GUM

DECYL GLUCOSIDE

PANTHENOL

GLYCERIN

LAURYL GLUCOSIDE

LECITHIN, SOYBEAN

METHYLISOTHIAZOLINONE

PHENOXYETHANOL

PROPYLENE GLYCOL

RESVERATROL

VITAMIN A PALMITATE

SODIUM METABISULFITE

ALPHA-TOCOPHEROL ACETATE

GLYCOL STEARATE

COCONUT OIL

PURPOSE

Anti-Itch Liquid

Keep out of reach of children. If swallowed, get medical help or contact a Poison Control Center right away.

INDICATIONS AND USAGE

Helps control the symptoms of scalp itch associated with minor skin irritations and rashes due to

- Seborrheic Dermatitis
- Eczema
- Psoriasis